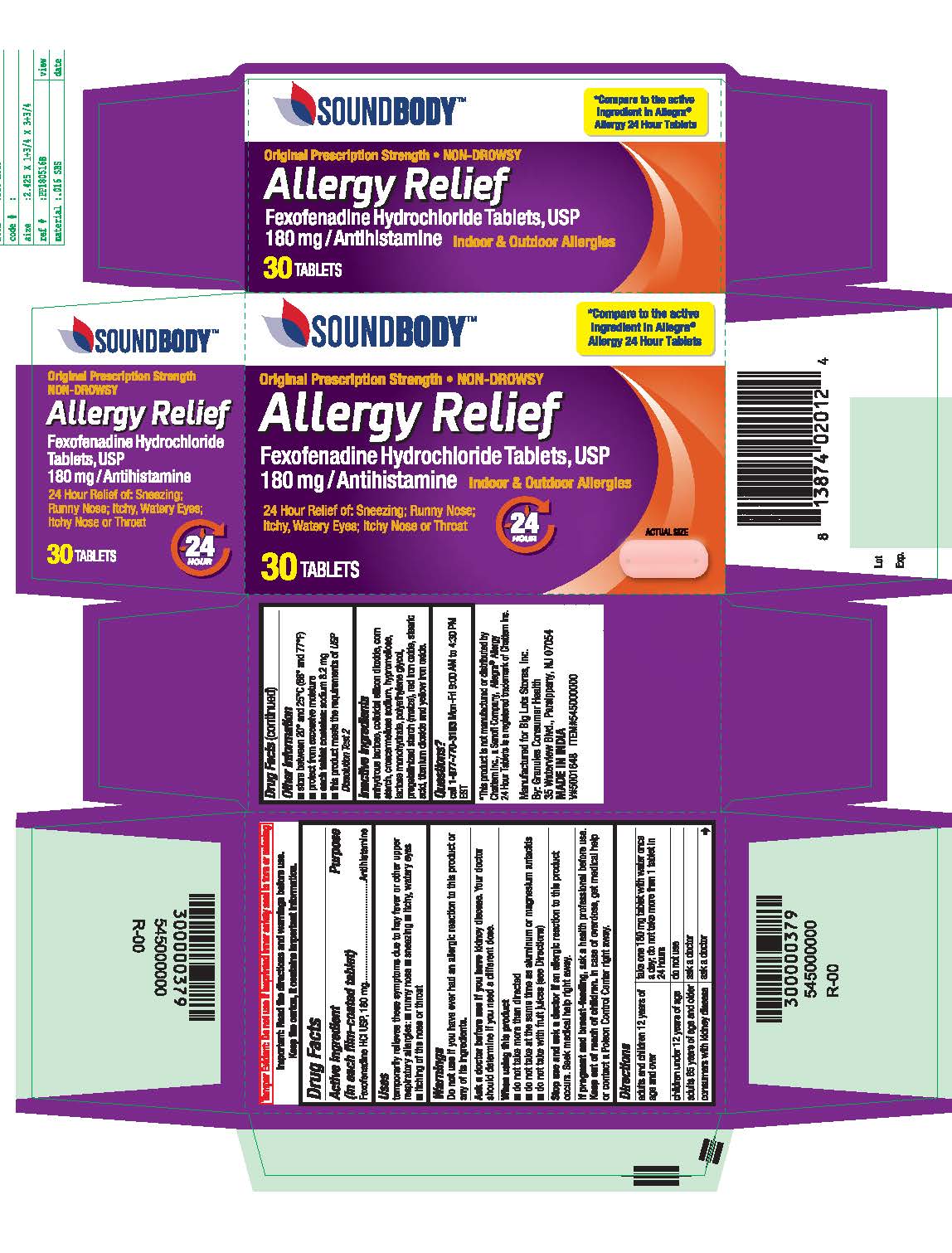 DRUG LABEL: Fexofenadine Hydrochloride
NDC: 50594-769 | Form: TABLET, FILM COATED
Manufacturer: Big Lots Stores, Inc.
Category: otc | Type: HUMAN OTC DRUG LABEL
Date: 20210129

ACTIVE INGREDIENTS: FEXOFENADINE HYDROCHLORIDE 180 mg/1 1
INACTIVE INGREDIENTS: TITANIUM DIOXIDE; CROSCARMELLOSE SODIUM; HYPROMELLOSES; ANHYDROUS LACTOSE; SILICON DIOXIDE; FERRIC OXIDE RED; LACTOSE MONOHYDRATE; POLYETHYLENE GLYCOL 400; STARCH, PREGELATINIZED CORN; STEARIC ACID; FERRIC OXIDE YELLOW

Original Prescription Strength
NON-DROWSY
Allergy Relief
Fexofenadine Hydrochloride Tablets, USP
180mg/Antihistamine
Indoor & Outdoor Allergies

Active ingredient

(in each film-coated tablet)

Fexofenadine HCl USP, 180 mg

Purpose

Antihistamine

Uses

temporarily relieves these symptoms due to hay fever or other upper respiratory allergies:

■ runny nose

■ sneezing

■ itchy, watery eyes

■ itching of the nose or throat

Do not use

if you have ever had an allergic reaction to this product or any of its ingredients.

Ask a doctor before use if you have

kidney disease. Your doctor should determine if you need a different dose.

When using this product

■ do not take more than directed

■ do not take at the same time as aluminum or magnesium antacids

■ do not take with fruit juices (see Directions)

Stop use and ask a doctor if

an allergic reaction to this product occurs. Seek medical help right away.

If pregnant or breast-feeding,

ask a health professional before use.

Keep out of reach of children.

In case of overdose, get medical help or contact a Poison Control Center right away.

Directions

adults and children 12 years of age and over

- take one 180mg tablet with water once a day; do not take more than 1 tablet in 24 hours

children under 12 years of age

- do not use

adults 65 years of age and older

- ask a doctor

consumers with kidney disease

- ask a doctor

Other Information

■ store between 20° and 25°C (68° and 77°F)

■ protect from excessive moisture

■ each tablet contains: sodium 8.2 mg

■ this product meets the requirements of USP Dissolution Test 2

Inactive ingredients

anhydrous lactose, colloidal silicon dioxide, corn starch, croscarmellose sodium, hypromellose, lactose monohydrate, polyethylene glycol, pregelatinized starch (maize), red iron oxide, stearic acid, titanium dioxide and yellow iron oxide.

Questions?

call 1-877-770-3183 Mon-Fri 9:00 AM to 4:30 PM EST.